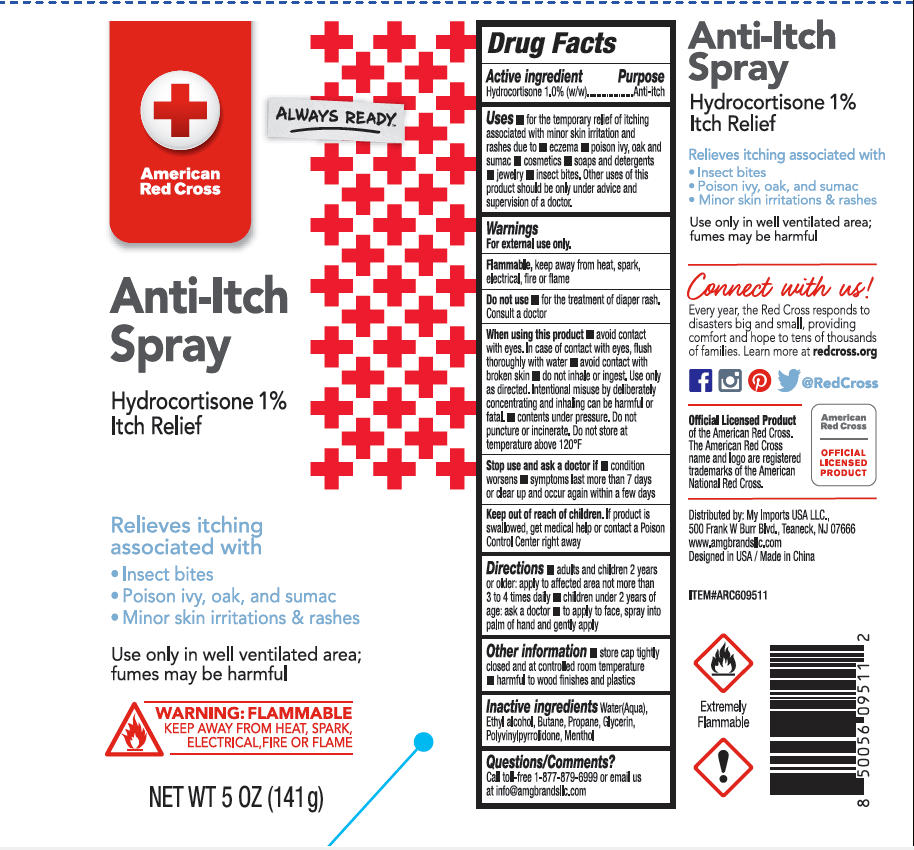 DRUG LABEL: American Red Cross Anti-Itch
NDC: 51628-4527 | Form: SPRAY
Manufacturer: MY IMPORTS USA LLC
Category: otc | Type: HUMAN OTC DRUG LABEL
Date: 20251027

ACTIVE INGREDIENTS: HYDROCORTISONE 1 g/100 g
INACTIVE INGREDIENTS: PROPANE; MENTHOL; ALCOHOL; GLYCERIN; POVIDONE; BUTANE; WATER

American Red Cross Anti-Itch Spray

Active ingredient

Hydrocortisone 1.0%(w/w)

Purpose

Anti-itch

Uses

- for the temporary relief of itching associated with minor skin irritation and rashes due to eczema,poison ivy, oak and sumac, cosmetics, soaps and detergents, jewelry, insect bites.
- Other uses of this product should be only under advice and supervision of a doctor.

Warnings

For external use only.

Flammable, keep away from heat, spark, electrical, fire or flame.

Do note use

Do nost use for the treatment of diaper rash. Consult a doctor.

When using this product

- avoid contact with eyes
- avoid contact with broken skin
- do not inhale or ingest. Use only as directed. Interntional misuse by deliberatebly concentrating and inhaling contents can be harmful or fatal.
- contents under pressure. Do not puncture or incinerate. Do not store at temperature above 120 ºF.

Stop use and ask a doctor if

- condition worsens
- symptoms last more than 7 days or clear up and occur again with a few days.

Keep out of reach of children

If swallowed, get medical help or contact a Poison Control Center right away.

Directions

- adults and children 2 years or older: apply to affected area not more than 3 to 4 times daily.
- children under 2 years of age: aks a doctor
- to apply to face, spray into palm of hand and gently apply.

Other information

- store cap tightly closed and at controlled room temperature
- harmful to wood finishes and plastics

Inactive ingredients

Water(Aqua)

Ethyl alcohol

Butane

Propane

Glycerin

Polyvinylpyrrolidone

Menthol